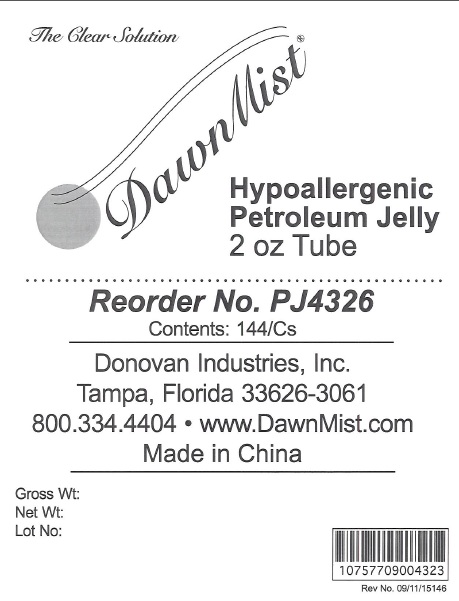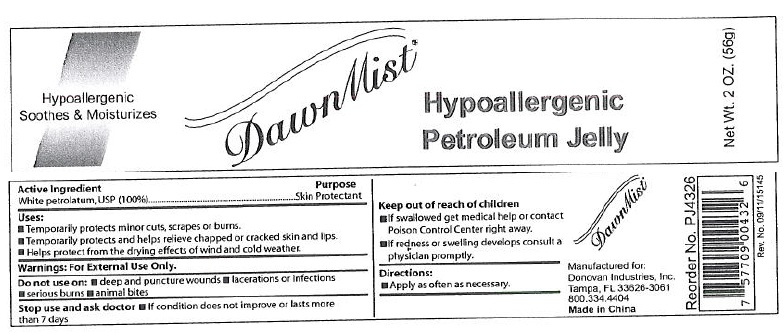 DRUG LABEL: DawnMist Hypoallergenic Petroleum
NDC: 55504-0432 | Form: JELLY
Manufacturer: Donovan Industries, Inc.
Category: otc | Type: HUMAN OTC DRUG LABEL
Date: 20110927

ACTIVE INGREDIENTS: PETROLATUM 100 g/100 g

DawnMist Hypoallergenic Petroleum Jelly

Active Ingredient

White Petrolatum, USP 100%

Purpose

Skin Protectant

Uses

- Temporarily protects minor cuts, scraps or burns
- Temporarily protects ad helps relieve chapped or cracked skin and lips.
- Helps protect from the drying effects of wind and cold weather

Warnings:

For external use only.

Do not use on:

- deep puncture wounds
- lacerations or infections
- serious burns
- animal bites

Stop use and ask doctor

- if condition does not improve or lasts more than 7 days

Keep out of reach of children.

- If swallowed get medical help or contact Poison Control Center right away
- If redness or swelling develops, consult a physician promptly

Directions

Apply as often as necessary.

Inactive Ingredients

none

Manufactured for:
Donovan Industries, Inc.
Tampa, FL 33623-3061
800.334.4404
Made in China

PACKAGE LABEL

Hypoallergenic

Soothes and Moisturizes

DawnMist

Hypoallergenic Petroleum Jelly